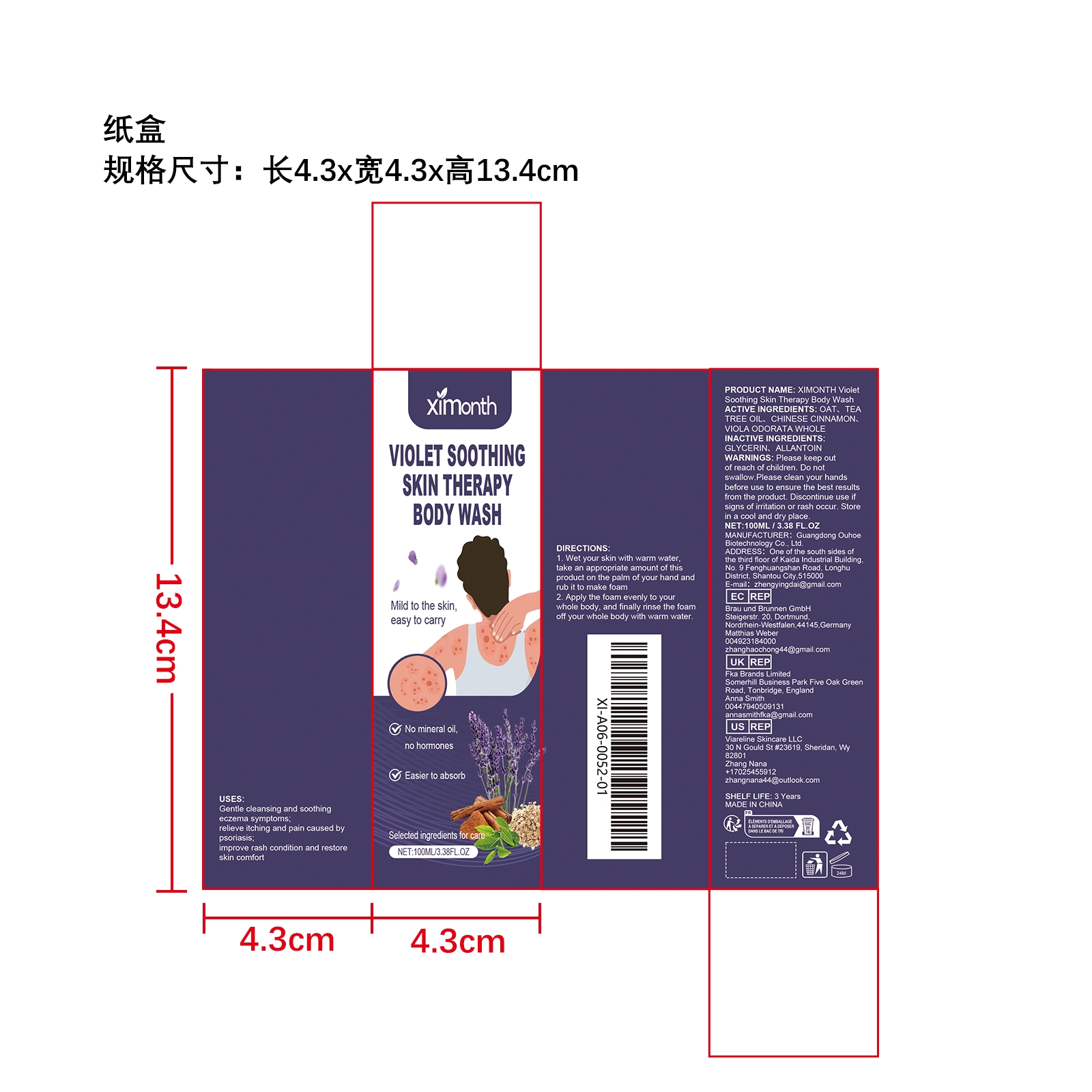 DRUG LABEL: XIMONTH Violet Soothing Skin Therapy Body Wash
NDC: 84744-067 | Form: LIQUID
Manufacturer: Guangdong Ouhoe Biotechnology Co., Ltd.
Category: otc | Type: HUMAN OTC DRUG LABEL
Date: 20241028

ACTIVE INGREDIENTS: CHINESE CINNAMON 15 mg/100 mg; TEA TREE OIL 10 mg/100 mg; VIOLA ODORATA WHOLE 15 mg/100 mg; OAT 30 mg/100 mg
INACTIVE INGREDIENTS: GLYCERIN 15 mg/100 mg; ALLANTOIN 15 mg/100 mg

ACTIVE INGREDIENTS

OAT、TEA TREE OIL、CHINESE CINNAMON、VIOLA ODORATA WHOLE

PURPOSE

Gentle cleansing and soothing eczema symptoms;relieve itching and pain caused by psoriasis;improve rash condition and restore skin comfort

USE

1. Wet your skin with warm water, take an appropriate amount of this product on the palm of your hand and rub it to make foam

2. Apply the foam evenly to your whole body, and finally rinse the foam off your whole body with warm water.

WARNINGS

Please keep outof reach of children. Do not swallow.Please clean your hands before use to ensure the best results from the product. Discontinue use if signs of irritation or rash occur. Store in a cool and dry place.

STOP USE

Discontinue use if signs of irritation or rash occur.

DO NOT USE

Discontinue use if signs of irritation or rash occur.

KEEP OUT OF REACH OF CHILDREN

Please keep outof reach of children. Do not swallow.

STORAGE AND HANDLING

Store in a cool and dry place.

INACTIVE INGREDIENT

GLYCERIN、ALLANTOIN